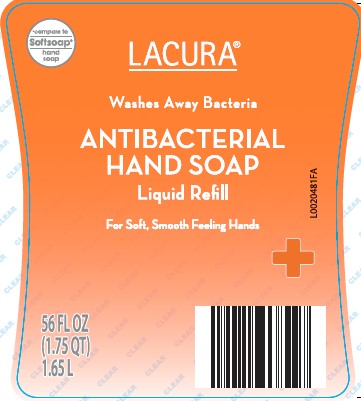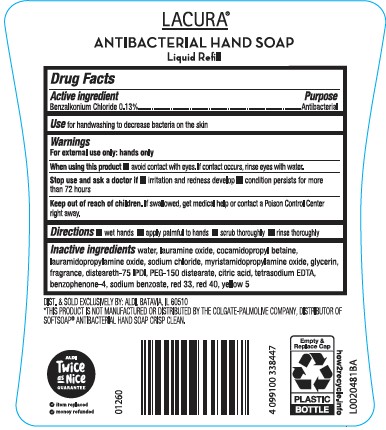 DRUG LABEL: Moisturizing Antibacterial
NDC: 64024-279 | Form: SOAP
Manufacturer: Aldi, LLC
Category: otc | Type: HUMAN OTC DRUG LABEL
Date: 20260129

ACTIVE INGREDIENTS: BENZALKONIUM CHLORIDE 1.3 mg/1 mL
INACTIVE INGREDIENTS: FD&C RED NO. 40; FD&C YELLOW NO. 5; WATER; LAURAMINE OXIDE; COCAMIDOPROPYL BETAINE; LAURAMIDOPROPYLAMINE OXIDE; SODIUM CHLORIDE; MYRISTAMIDOPROPYLAMINE OXIDE; GLYCERIN; DISTEARETH-75 ISOPHORONE DIISOCYANATE; PEG-150 DISTEARATE; CITRIC ACID MONOHYDRATE; EDETATE SODIUM; SULISOBENZONE; SODIUM BENZOATE; D&C RED NO. 33

Lacura 279.003/279AD
Antibacterial Liquid Hand Soap

Claims

LACURA

ANTIBACTERIAL HAND SOAP

Liquid Refill

Active Ingredient

Benzalkonium chloride 0.13%

Purpose

Antibacterial

Use

for handwashing to decrease bacteria on the skin

Warnings

For external use only: hands only

When using this product

avoid contact with eyes. If contact occurs, rinse eyes with water.

Stop use and ask a doctor if

- irritation and redness develop
- condition persists for more than 72 hours

Keep out of reach of children.

If swallowed, get medical help or contact a Poison Control Center right away.

Directions

- wet hands
- apply palmful to hands
- scrub thoroughly
- rinse thoroughly

Inactive ingredients

water, lauramine oxide, cocamidopropyl betaine, lauramidopropylamine oxide, sodium chloride, myristamidopropylamine oxide, glycerin, fragrance, disteareth-75 IPDI, PEG-150 distearate, citric acid, tetrasodium EDTA, benzophenone-4, sodium benzoate, red 33, red 40, yellow 5

ADVERSE REACTION

DIST. & SOLD EXCLUSIVELY BY: ALDI, BATAVIA, IL 60510

ALDI Twice as Nice Guarantee

- item replaced
- money refunded

how2recycle.info

empty & replace cap

plastic bottle

Disclaimer

*THIS PRODUCT IS NOT MANUFACTURED OR DISTRIBUTED BY THE COLGATE-PALMOLIVE COMPANY, DISTRIBUTER OF SOFTSOAP®ANTIBACTERIAL HAND SOAP CRISP CLEAN.

Principal Panel Display

*Compare to Softsoap ®hand soap

LACURA®

Washes Away Bacteria

ANTIBACTERIAL HAND SOAP

Liquid Refill

For Soft, Smooth Feeling Hands

56 FL OZ (1.75 QT) 1.65 L